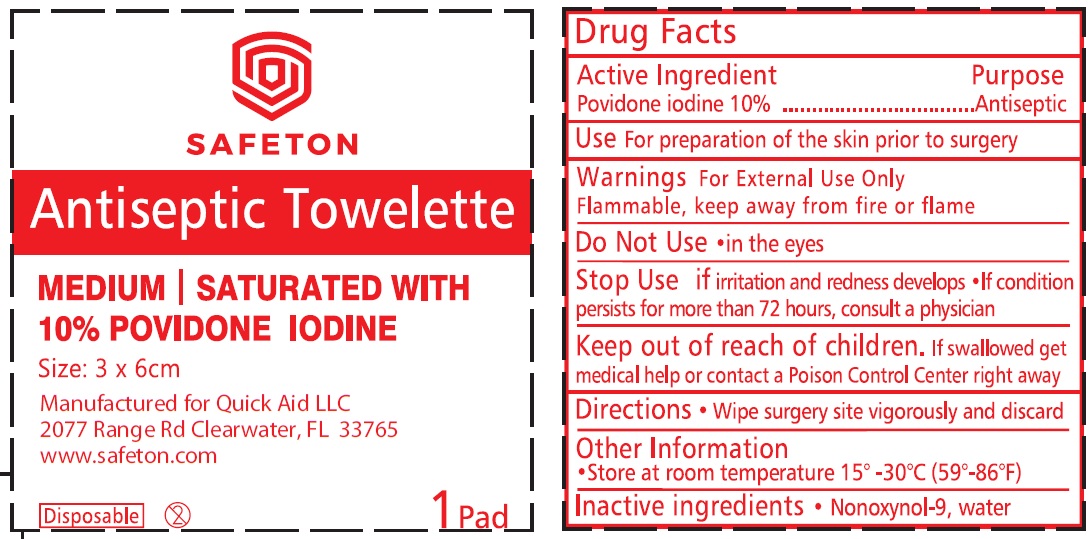 DRUG LABEL: Safeton Antiseptic Towelette 10 Povidone Iodine
NDC: 83006-001 | Form: SWAB
Manufacturer: QUICK AID LLC
Category: otc | Type: HUMAN OTC DRUG LABEL
Date: 20221019

ACTIVE INGREDIENTS: POVIDONE-IODINE 100 mg/1 g
INACTIVE INGREDIENTS: NONOXYNOL-9; WATER

Safeton Antiseptic Towelette 10% Povidone Iodine

Active Ingredient

Povidone iodine 10%

Purpose

Antiseptic

Use

For preparation of the skin prior to surgery

Warnings

For External Use Only

Flammable, keep away from fire or flame

Do Not Use

- in the eyes

Stop Use

if irritation and redness develops

- If condition persists for more than 72 hours, consult a physician

Keep out of reach of children.

- If swallowed get medical help or contact a Poison Control Center right away

Directions

- Wipe surgery site vigorously and discard

Other Information

- Store at room temperature 15°-30°C (59°-86°F)

Inactive ingredients

- Nonoxynol-9, water